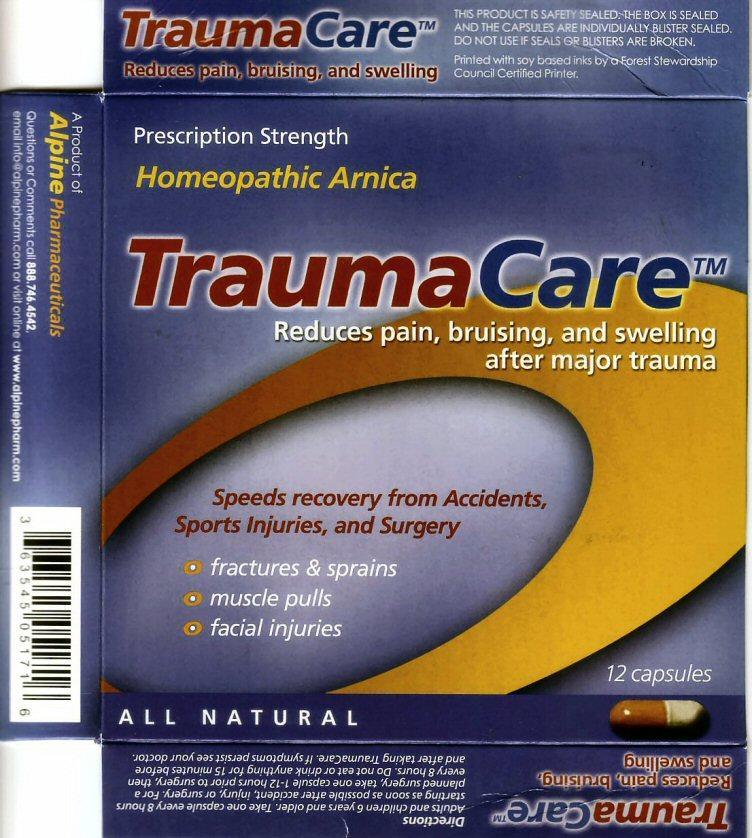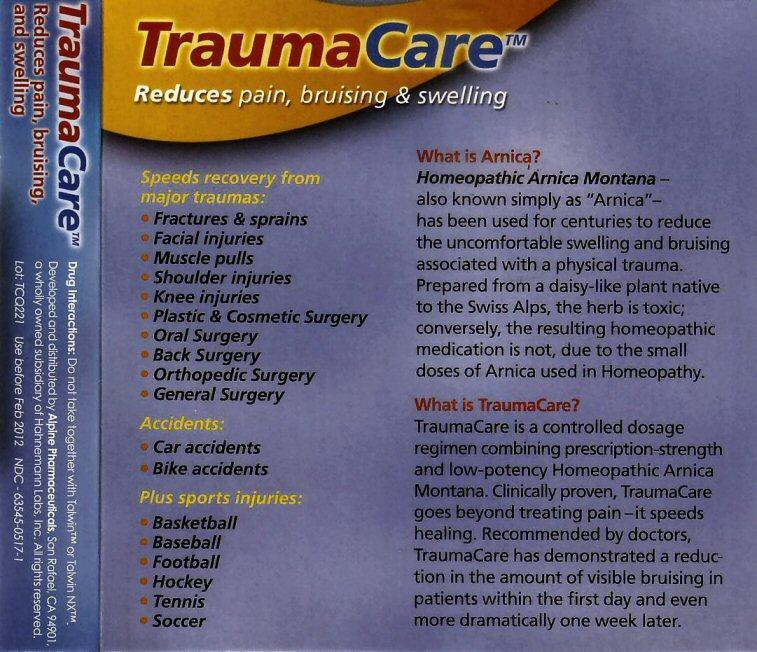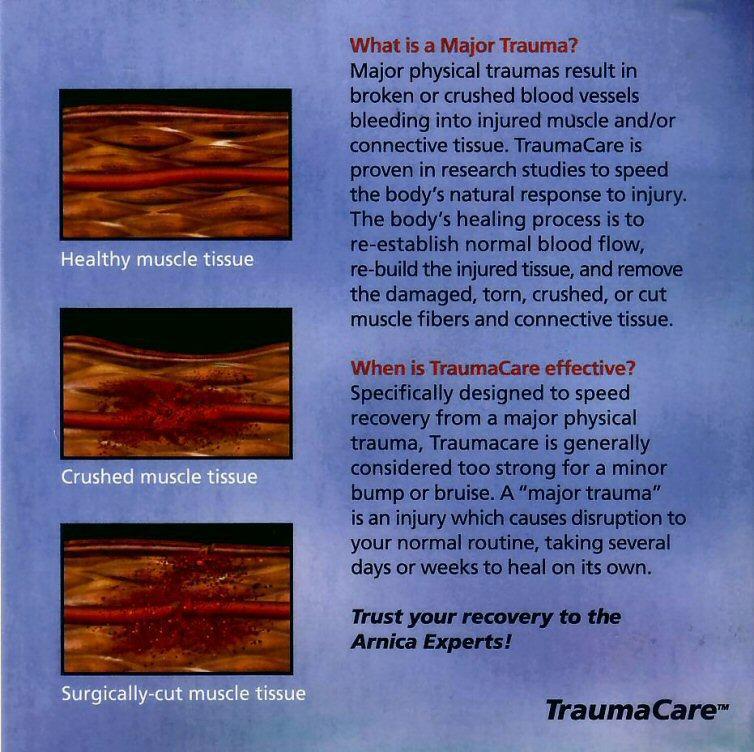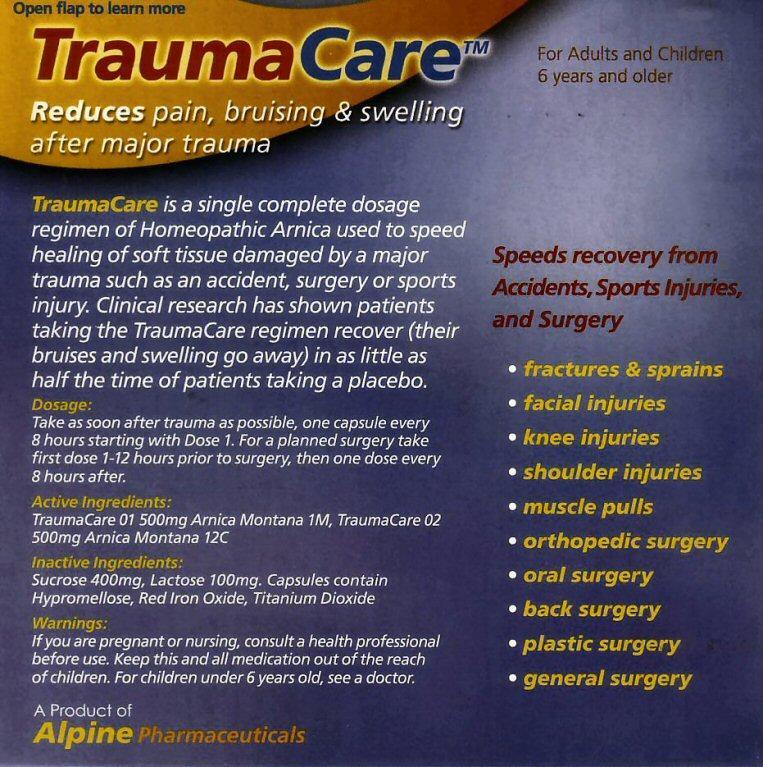 DRUG LABEL: TraumaCare
NDC: 63545-517 | Form: CAPSULE
Manufacturer: Hahnemann Laboratories, Inc. dba Alpine Pharmaceuticals
Category: homeopathic | Type: HUMAN OTC DRUG LABEL
Date: 20120114

ACTIVE INGREDIENTS: ARNICA MONTANA 1 [hp_M]/1 1
INACTIVE INGREDIENTS: SUCROSE; LACTOSE; HYPROMELLOSES; FERRIC OXIDE RED; TITANIUM DIOXIDE

Active Ingredients

TraumaCare 01 500mg Arnica Montana 1M, TraumaCare 02 500mg Arnica Montana 12C

Purpose

Speeds recovery from Accidents, Sports Injuries, and Surgery

- fractures and sprains
- muscle pulls
- facial injuries

Reduces pain, bruising, and swelling after major trauma

Keep Out of Reach of Children

Keep this and all medication out of the reach of children.

Uses

Reduces pain, bruising, and swelling after major trauma.

TraumaCare is a single complete dosage regimen of Homeopathic Arnica used to speed healing of soft tissue damaged by a major trauma such as an accident, surgery or sports injury. Clinical research has shown patients taking the TraumaCare regimen recover (their bruises and swelling go away) in as little as half the time of patients taking a placebo.

Warnings

If you are pregnant or nursing, consult a health professional before use. For children under 6 years old, see a doctor.

Drug Interactions

Drug Interactions: Do not take together with Talwin tm or Talwin NX tm

Directions

Adults and children 6 years and older. Take one capsule every 8 hours starting as soon as possible after accident, injury, or surgery. For a planned surgery, take one capsule 1-12 hours prior to surgery, then every 8 hours. Do not eat or drink anything for 15 minutes minutes before and after taking TraumaCare. If symptoms persist see your doctor.

Additional Information About Product

What is Arnica?

Homeopathic Arnica Montana - also known simply as "Arnica" - has been used for centuries to reduce the uncomfortable swelling and bruising associated with a physical trauma. Prepared from a daisy-like plant native to the Swiss Alps, the herb is toxic; conversely, the resulting homeopathic medication is not, due to the small doses of Arnica used in Homeopathy.

What is TraumaCare?

TraumaCare is a controlled dosage regimen combining prescription-strength and low-potency Homeopathic Arnica Montana. Clinically proven, TraumaCare goes beyond treating pain - it speeds healing. Recommended by doctors, TraumaCare has demonstrated a reduction in the amount of visible bruising in patients within the first day and even more dramatically one week later.

What is a Major Trauma?

Major physical traumas result in broken or crushed blood vessels bleeding into injured muscle and/or connective tissue. TraumaCare is proven in research studies to speed the body's natural response to injury. The body's healing process is to re-establish normal blood flow, re-build the injured tissue, and remove the damaged, torn, crushed, or cut muscle fibers and connective tissue.

When is TraumaCare effective?

Specifically designed to speed recovery from a major physical trauma, Traumacare is generally considered too strong for a minor bump or bruise. A "major trauma" is an injury which causes disruption to your normal routine, taking several days or weeks to heal on its own.

Trust your recovery to the Arnica Experts!

TraumaCare TM

Inactive Ingredients

Inactive Ingredients : Sucrose 400mg, Lactose 100 mg, Capsules contain Hypromellose, Red Iron Oxide, Titanium Dioxide

Package Label

TraumaCare TM Reduces pain, bruising, and major swelling after major trauma

Prescription Strength Homeopathic Arnica

Speeds recovery from Accidents, Sports Injuries, and Surgery

Speeds recovery from major traumas:

- fractures and sprains
- muscle pulls
- facial injuries
- knee injuries
- shoulder injuries
- orthopedic surgery
- oral surgery
- back surgery
- plastic surgery
- general surgery

Accidents:

- Car accidents
- bike accidents

Plus sports injuries:

- Basketball
- Baseball
- Football
- Hockey
- Tennis
- Soccer

THIS PRODUCT IS SAFETY SEALED. THE BOX IS SEALED AND THE CAPSULES ARE INDIVIDUALLY BLISTER SEALED.DO NOT USE IF SEALS OR BLISTERS ARE BROKEN.
Printed with soy based inks by a Forest Stewardship Council Certified Printer.
Developed and distributed by Alpine Pharmaceuticals, San Rafael, CA 94901 a wholly owned subsidiary of Hahnemann Laboratories, Inc. All rights reserved.
Lot:TCQ221 Use before Feb 2012 NDC 63545-517-01
A Product of Alpine Pharmaceuticals
Questions or Comments call 888-746-4542 email info@alpinepharma.com or visit online at www.alpinepharma.com
ALL NATURAL 12 capsules For Adults and Children 6 years and older